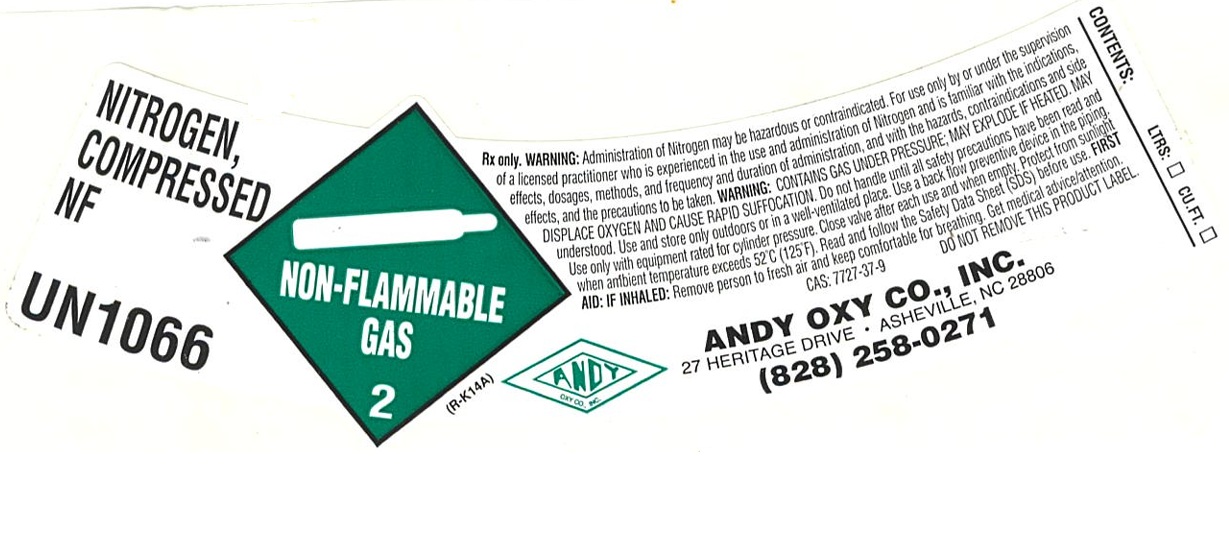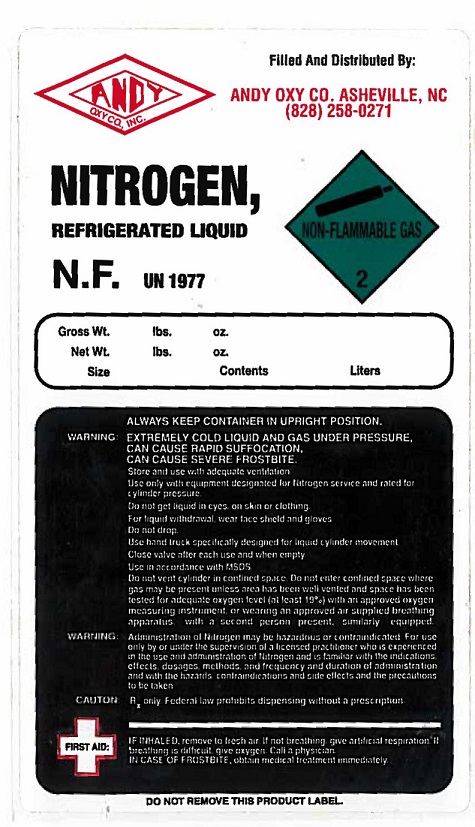 DRUG LABEL: Nitrogen
NDC: 50063-002 | Form: GAS
Manufacturer: Andy-Oxy Co., Inc.
Category: prescription | Type: HUMAN PRESCRIPTION DRUG LABEL
Date: 20251030

ACTIVE INGREDIENTS: NITROGEN 992 mL/1 L

Nitrogen

PACKAGE LABEL

Filled and Distributed By: ANDY OXY CO. ASHEVILLE, NC (828) 258-0271 NITROGEN, REFRIGERATED LIQUID NON-FLAMMABLE GAS 2 N.F. UN 1977 Gross Wt. lbs. oz. Net Wt. lbs. oz. Size Contents Liters WARNING: ALWAYS KEEP CONTAINER IN UPRIGHT POSITION. EXTREMELY COLD LIQUID AND GAS UNDER PRESSURE, CAN CAUSE RAPID SUFFOCATION, CAN CAUSE SEVERE FROSTBITE, Store and use with adequate ventilation, Use only with equipment designated for Nitrogen service and rated for cylinder pressure. Do not get liquid in eyes, on skin or clothing. For liquid withdrawal, wear face shield and gloves. Do not drop. Use hand truck specifically designed for liquid cylinder movement. Close valve after each use and when empty. Use in accordance with MSDS. Do not vent cylinder in confined space. Do not enter confined space where gas may be present unless area has been well vented and space has been tested for adequate oxygen level (at least 19%) with ana pproved oxygen measuring instrument, or wearing an approved air supplied breathing apparatus, with a second person present, similarly equipped. WARNING: Administration of Nitrogen may be hazardous or contraindicated. For use only by or under the supervision of a licensed practitioner who is experienced in the use and administration of nitrogen and is familiar with the indications, effects, dosages, methods, and frequency and duration of administration and with the hazards, contraindications and side effects and the precautions to be taken. CAUTION: Rx only. Federal law prohibits dispensing without a prescription. FIRST AID: IF INHALED, remove to fresh air. If not breathing, give artificial respiration. If breathing is difficult, give oxygen. Call a physician. IN CASE OF FROSTBITE, obtain medical treatmen immediately. DO NOT REMOVE THIS PRODUCT LABEL.

PACKAGE LABEL

NITROGEN, COMPRESSED NF

UN1066

Rx only. WARNING: Administration of Nitrogen may be hazardous or contraindicated. For use only by or under the supervision of a licensed practitioner who is experienced in the use and administration of Nitrogen and is familiar with the indications, effects, dosages, methods, and frequency and duration of administration, and with the hazards, contraindications and side effects, and the precautions to be taken. WARNING: CONTAINS GAS UNDER PRESSURE; MAY EXPLODE IF HEATED. MAY DISPLACE OXYGEN AND CAUSE RAPID SUFFOCATION. Do not handle until all safety precautions have been read and understood. Use and store only outdoors or in a well-ventilated place. Use a back flow preventive device in the piping. Use only with equipment rated for cylinder pressure. Close valve after each use and when empty. Protect from sunlight when ambient temperature exceeds 52 C (125 F). Read and follow the Safety Data Sheet (SDS) before use. FIRST AID: IF INHALED: Remove person to fresh air and keep comfortable for breathing. Get medical advice/attention.

CAS: 7727-37-9 DO NOT REMOVE THIS PRODUCT LABEL.

ANDY OXY CO., INC

27 HERITAGE DR. ASHEVILLE, NC 28806

(828) 258-0271

CONTENTS: LTRS: CU.FT.